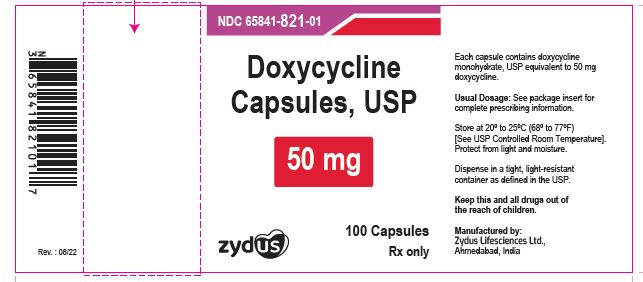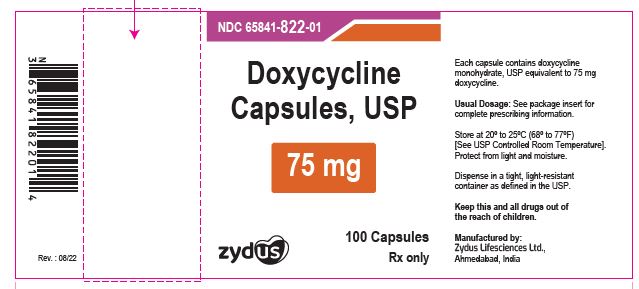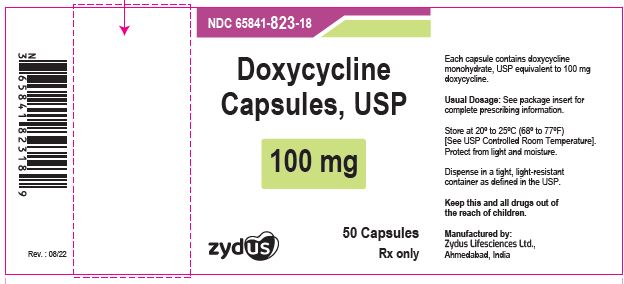 DRUG LABEL: doxycycline
NDC: 65841-821 | Form: CAPSULE
Manufacturer: Zydus Lifesciences Limited
Category: prescription | Type: HUMAN PRESCRIPTION DRUG LABEL
Date: 20241128

ACTIVE INGREDIENTS: DOXYCYCLINE 50 mg/1 1
INACTIVE INGREDIENTS: SILICON DIOXIDE; GELATIN; MAGNESIUM STEARATE; CELLULOSE, MICROCRYSTALLINE; SODIUM LAURYL SULFATE; SODIUM STARCH GLYCOLATE TYPE A POTATO; TITANIUM DIOXIDE; FERRIC OXIDE YELLOW; FERROSOFERRIC OXIDE; POTASSIUM HYDROXIDE; PROPYLENE GLYCOL; SHELLAC; AMMONIA

Doxycycline Capsules, USP

PACKAGE LABEL.PRINCIPAL DISPLAY PANEL

NDC 65841-821-01 in bottle of 100 Capsules

Doxycycline Capsules USP, 50 mg

Rx Only

100 Capsules

NDC 65841-822-01 in bottle of 100 Capsules

Doxycycline Capsules USP, 75 mg

Rx Only

100 Capsules

NDC 65841-823-01 in bottle of 100 Capsules

Doxycycline Capsules USP, 100 mg

Rx Only

100 Capsules